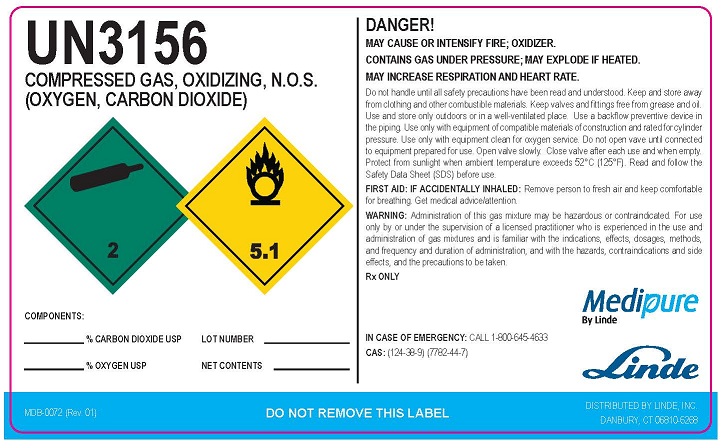 DRUG LABEL: Carbon Dioxide Oxygen Mix
NDC: 59579-008 | Form: GAS
Manufacturer: Linde Gas & Equipment Inc.
Category: prescription | Type: HUMAN PRESCRIPTION DRUG LABEL
Date: 20251219

ACTIVE INGREDIENTS: CARBON DIOXIDE 300 mL/1 L; OXYGEN 700 mL/1 L

Carbon Dioxide/Oxygen mixture

PACKAGE LABEL

UN3156

COMPRESSED GAS,

OXIDIZING, N.O.S.

(OXYGEN, CARBON DIOXIDE)

COMPONENTS:

_____________% CARBON DIOXIDE USP LOT NUMBER
_____________% OXYGEN USP NET CONTENTS

DANGER!

MAY CAUSE OR INTENSIFY FIRE; OXIDIZER.
CONTAINS GAS UNDER PRESSURE; MAY EXPLODE IF HEATED.
MAY INCREASE RESPIRATION AND HEART RATE.

Do not handle until all safety precautions have been read and understood. Keep and store away from clothing and other combustible materials. Keep valves and fittings free from grease and oil. Use and store only outdoors or in a well-ventilated place. Use a backflow preventive device in the piping. Use only with equipment of compatible materials of construction and rated for cylinder pressure. Use only with equipment clean for oxygen service. Do not open valve until connected to equipment prepared for use. Open valve slowly. Close valve after each use and when empty. Protect from sunlight when ambient temperature exceeds 52°C (125°F). Read and follow the Safety Data Sheet (SDS) before use.

FIRST AID: IF ACCIDENTALLY INHALED: Remove person to fresh air and keep comfortable for breathing. Get medical advice/attention.

WARNING: Administration of this gas mixture may be hazardous or contraindicated. For use only by or under the supervision of a licensed practitioner who is experienced in the use and administration of gas mixtures and is familiar with the indications, effects, dosages, methods, and frequency and duration of administration, and with the hazards, contraindications and side effects, and the precautions to be taken.
Rx ONLY

IN CASE OF EMERGENCY CALL 1-800-645-4633

CAS: (124-38-9) (7782-44-7)

MDB-0072 (Rev. 01)
DO NOT REMOVE THIS LABEL
DISTRIBUTED BY LINDE, INC.
DANBURY, CT 06810-6268